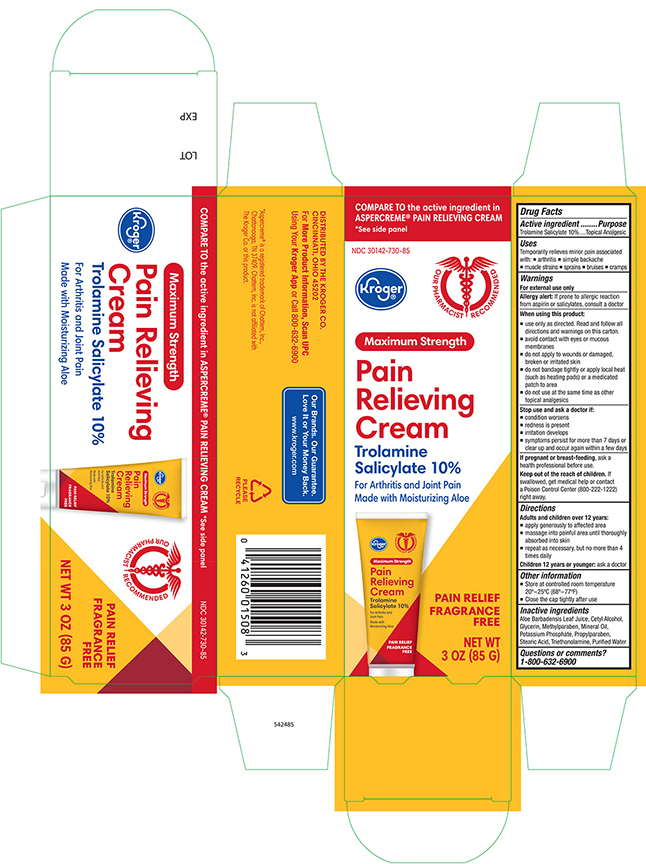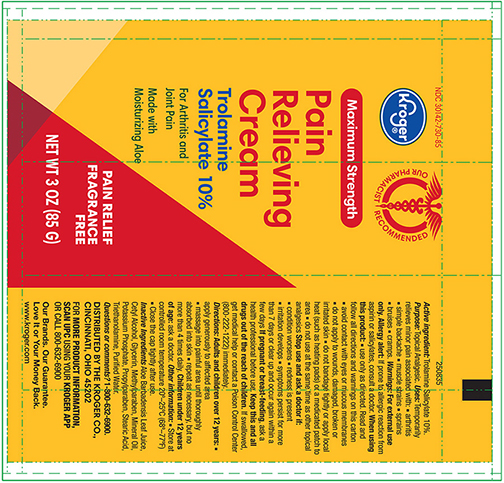 DRUG LABEL: Kroger Odor Free Arthricream Rub Pain Relieving
NDC: 30142-730 | Form: CREAM
Manufacturer: THE KROGER CO
Category: otc | Type: HUMAN OTC DRUG LABEL
Date: 20220425

ACTIVE INGREDIENTS: TROLAMINE SALICYLATE 100 mg/1 g
INACTIVE INGREDIENTS: ALOE VERA LEAF; CETYL ALCOHOL; GLYCERIN; METHYLPARABEN; MINERAL OIL; POTASSIUM PHOSPHATE, MONOBASIC; PROPYLPARABEN; STEARIC ACID; TROLAMINE; WATER

Active Ingredient

Trolamine Salicylate 10%

Purpose

Topical analgesic

Uses

temporary relieves minor pain associated with:

- arthritis
- simple backache
- muscle strains
- sprains
- bruises
- cramps

Warnings

For external use only

Allergy alert If prone to allergic reaction from aspirin or salicylates, consult a doctor before use.

When using this product

- use only as directed. Read and follow all directions and warnings on this label.
- do not bandage tightly or apply local heat (such as heating pads) to the area of use
- avoid contact with eyes or mucous membranes
- do not apply to wounds or damaged, broken or irritated skin
- do not use at the same time as other topical analgesics

Stop use and ask a doctor if;

- condition worsens
- symptoms persist for more than 7 days or clear up and occur again within a few days
- redness is present
- irritation develops

If pregnant or breast-feeding,

ask a health professional before use.

Keep out of reach of children.

If swallowed, get medical help or contact a Poison Control Center right away.

Directions Adults and children over 12

- apply generously to affected area
- massage into painful area until thoroughly absorbed into skin
- repeat as necessary, but no more than 3 to 4 times daily

children 12 years and younger: ask a doctor

Other information

Store at controlled room temperature 20- 25°C (68 - 77°F)

Close the cap tightly after use

Inactive ingredient

Aloe Barbadensis Leaf Juice, Cetyl Alcohol, Glycerin, Methylparaben, Mineral Oil, Potassium Phosphate, Propylparaben, Stearic Acid, Triethanolamine, Water (purified)

Principal Primary Panel -Tube

Kroger NDC 30142-730-85

Maximum Strength

PAIN RELIEVING CREAM

Trolamine Salicylate 10%

NET WT 3 OZ (85 G)

Principal Primary Panel -Carton

Kroger NDC 30142-730-85
Maximum Strength

PAIN RELIEVING CREAM

Trolamine Salicylate 10%

NET WT 3 OZ (85 G)